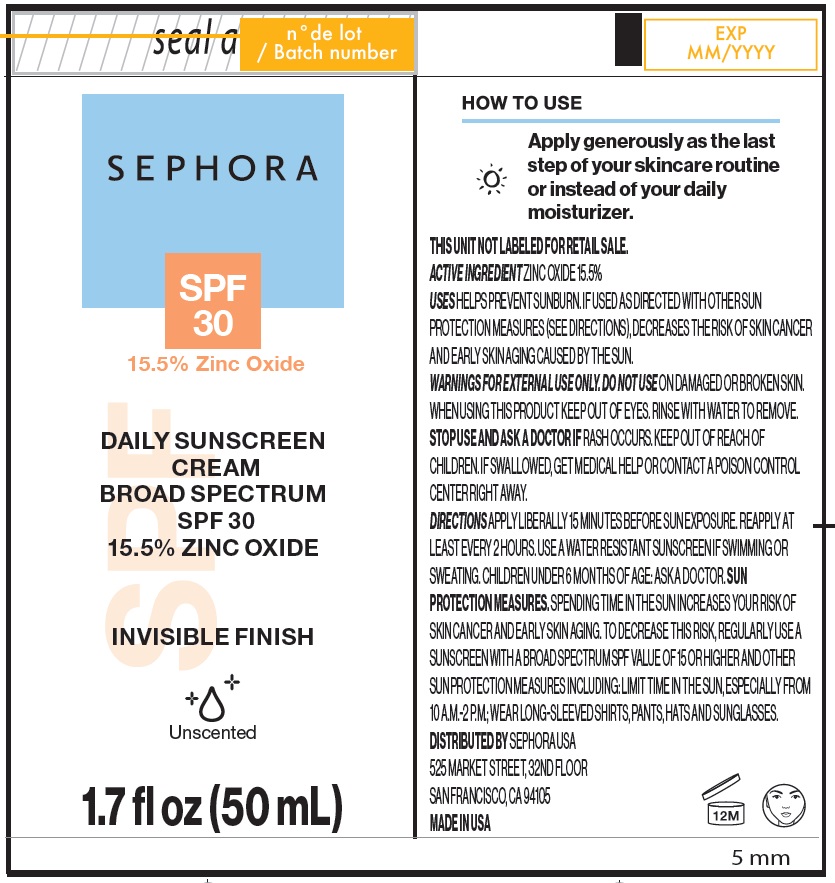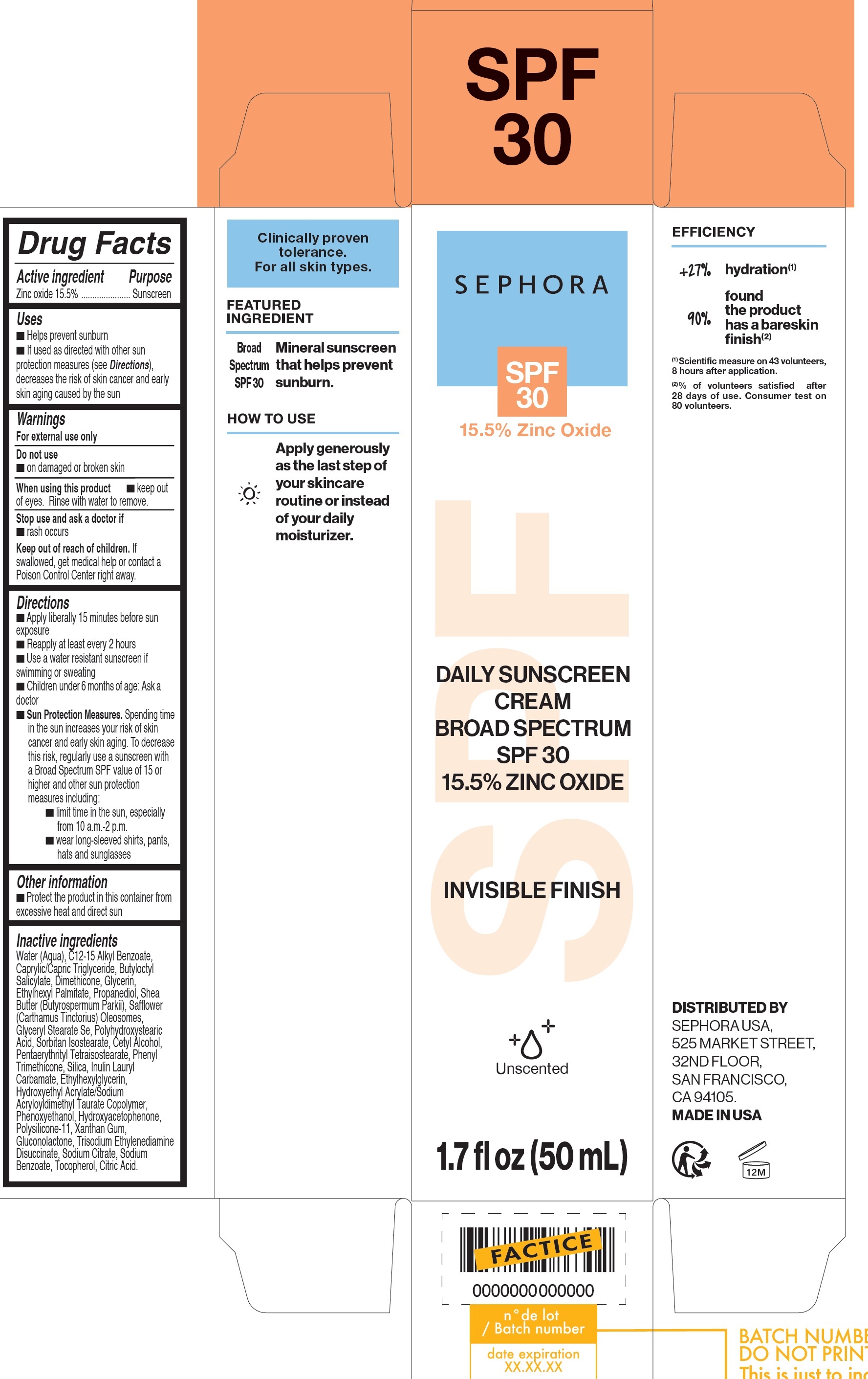 DRUG LABEL: DAILY SUNSCREEN BROAD SPECTRUM SPF 30
NDC: 31720-231 | Form: CREAM
Manufacturer: S+
Category: otc | Type: HUMAN OTC DRUG LABEL
Date: 20260209

ACTIVE INGREDIENTS: ZINC OXIDE 155 mg/1 mL
INACTIVE INGREDIENTS: WATER; ALKYL (C12-15) BENZOATE; MEDIUM-CHAIN TRIGLYCERIDES; BUTYLOCTYL SALICYLATE; DIMETHICONE; GLYCERIN; ETHYLHEXYL PALMITATE; PROPANEDIOL; SHEA BUTTER; CARTHAMUS TINCTORIUS SEED OLEOSOMES; GLYCERYL STEARATE SE; SORBITAN ISOSTEARATE; CETYL ALCOHOL; PENTAERYTHRITYL TETRAISOSTEARATE; PHENYL TRIMETHICONE; SILICON DIOXIDE; INULIN LAURYL CARBAMATE; ETHYLHEXYLGLYCERIN; PHENOXYETHANOL; HYDROXYACETOPHENONE; DIMETHICONE/VINYL DIMETHICONE CROSSPOLYMER (SOFT PARTICLE); XANTHAN GUM; GLUCONOLACTONE; TRISODIUM ETHYLENEDIAMINE DISUCCINATE; SODIUM CITRATE, UNSPECIFIED FORM; SODIUM BENZOATE; TOCOPHEROL; CITRIC ACID MONOHYDRATE

DAILY SUNSCREEN CREAM BROAD SPECTRUM SPF 30

Active ingredient

Zinc oxide 15.5%

Purpose

Sunscreen

Uses

- Helps prevent sunburn
- If used as directed with other sun protection measures (see Directions), decreases the risk of skin cancer and early skin aging caused by the sun

Warnings

For external use only

Do not use

- on damaged or broken skin

When using this product

- keep out of eyes. Rinse with water to remove.

Stop use and ask a doctor if

- rash occurs

Keep out of reach of children.

If swallowed, get medical help or contact a Poison Control Center right away.

Directions

- Apply liberally 15 minutes before sun exposure
- Reapply at least every 2 hours
- Use a water resistant sunscreen if swimming or sweating
- Children under 6 months of age: Ask a doctor
- Sun Protection Measures.Spending time in the sun increases your risk of skin cancer and early skin aging. To decrease this risk, regularly use a sunscreen with a Broad Spectrum SPF value of 15 or higher and other sun protection measures including:
- limit time in the sun, especially from 10 a.m.-2 p.m.
- wear long-sleeved shirts, pants, hats and sunglasses

Other information

- Protect the product in this container from excessive heat and direct sun

Inactive ingredients

Water (Aqua), C12-15 Alkyl Benzoate, Caprylic/Capric Triglyceride, Butyloctyl Salicylate, Dimethicone, Glycerin, Ethylhexyl Palmitate, Propanediol, Shea Butter (Butyrospermum Parkii), Safflower (Carthamus Tinctorius) Oleosomes, Glyceryl Stearate Se, Polyhydroxystearic Acid, Sorbitan Isostearate, Cetyl Alcohol, Pentaerythrityl Tetraisostearate, Phenyl Trimethicone, Silica, Inulin Lauryl Carbamate, Ethylhexylglycerin, Hydroxyethyl Acrylate/Sodium Acryloyldimethyl Taurate Copolymer, Phenoxyethanol, Hydroxyacetophenone, Polysilicone-11, Xanthan Gum, Gluconolactone, Trisodium Ethylenediamine Disuccinate, Sodium Citrate, Sodium Benzoate, Tocopherol, Citric Acid.